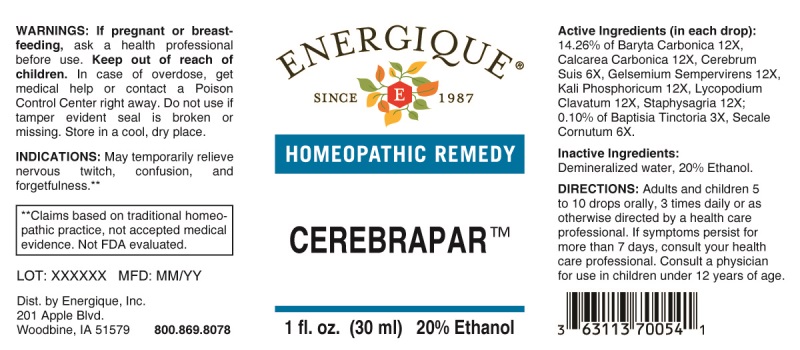 DRUG LABEL: Cerebrapar
NDC: 44911-0317 | Form: LIQUID
Manufacturer: Energique, Inc.
Category: homeopathic | Type: HUMAN OTC DRUG LABEL
Date: 20241024

ACTIVE INGREDIENTS: BAPTISIA TINCTORIA ROOT 3 [hp_X]/1 mL; SUS SCROFA CEREBRUM 6 [hp_X]/1 mL; CLAVICEPS PURPUREA SCLEROTIUM 6 [hp_X]/1 mL; BARIUM CARBONATE 12 [hp_X]/1 mL; OYSTER SHELL CALCIUM CARBONATE, CRUDE 12 [hp_X]/1 mL; GELSEMIUM SEMPERVIRENS ROOT 12 [hp_X]/1 mL; POTASSIUM PHOSPHATE, DIBASIC 12 [hp_X]/1 mL; LYCOPODIUM CLAVATUM SPORE 12 [hp_X]/1 mL; DELPHINIUM STAPHISAGRIA SEED 12 [hp_X]/1 mL
INACTIVE INGREDIENTS: WATER; ALCOHOL

DRUG FACTS:

ACTIVE INGREDIENTS:

(in each drop): 14.26% of Baryta Carbonica 12X, Calcarea Carbonica 12X, Cerebrum Suis 6X, Gelsemium Sempervirens 12X, Kali Phosphoricum 12X, Lycopodium Clavatum 12X, Staphysagria 12X; 0.10% of Baptisia Tinctoria 3X, Secale Cornutum 6X.

INDICATIONS:

May temporarily relieve nervous twitch, confusion and forgetfulness.**

**Claims based on traditional homeopathic practice, not accepted medical evidence. Not FDA evaluated.

WARNINGS:

If pregnant or breastfeeding, ask a health professional before use.

Keep out of reach of children. In case of overdose, get medical help or contact a Poison Control Center right away.

Do not use if tamper evident seal is broken or missing.

Store in a cool, dry place.

Keep out of reach of children. In case of overdose, get medical help or contact a Poison Control Center right away.

DIRECTIONS:

Adults and children 5 to 10 drops orally, 3 times daily or as otherwise directed by a health care professional. If symptoms persist for more than 7 days, consult your health care professional. Consult a physician for use in children under 12 years of age.

INDICATIONS:

May temporarily relieve nervous twitch, confusion and forgetfulness.**

**Claims based on traditional homeopathic practice, not accepted medical evidence. Not FDA evaluated.

INACTIVE INGREDIENTS:

Demineralized water, 20% Ethanol.

QUESTIONS:

Dist. by Energique, Inc.
201 Apple Blvd.
Woodbine, IA 51579 800.869.8078

PACKAGE LABEL DISPLAY:

ENERGIQUE

SINCE 1987

HOMEOPATHIC REMEDY

CEREBRAPAR

1 fl. oz. (30 ml)